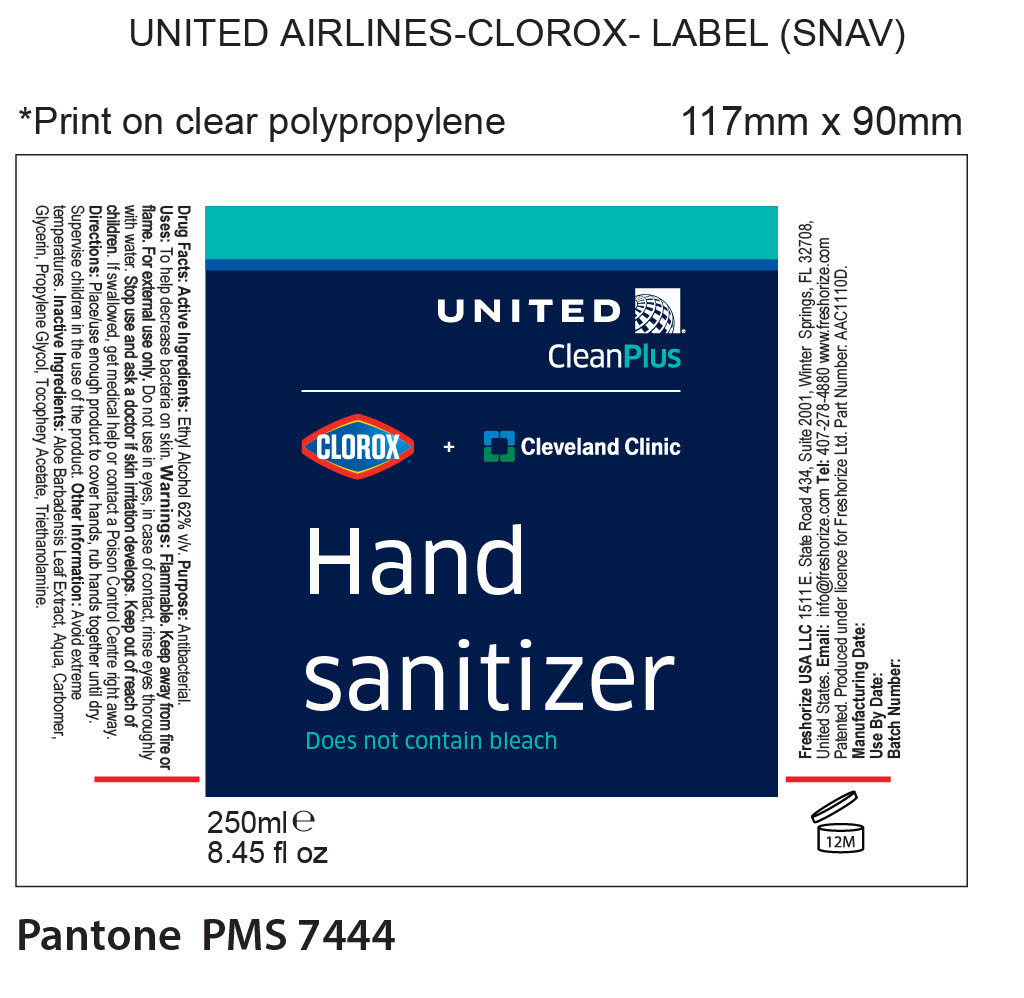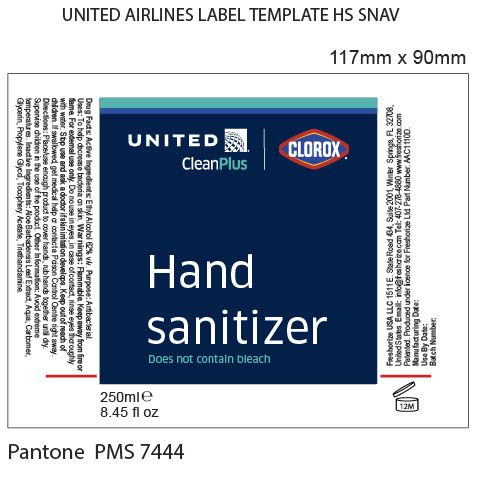 DRUG LABEL: United Airlines Clean Plus Clorox
NDC: 52305-225 | Form: LIQUID
Manufacturer: Freshorize LLC
Category: otc | Type: HUMAN OTC DRUG LABEL
Date: 20241017

ACTIVE INGREDIENTS: ALCOHOL 62 mL/100 mL
INACTIVE INGREDIENTS: PROPYLENE GLYCOL 0.001 mL/100 mL; CARBOMER 934 0.28 mL/100 mL; ALOE VERA LEAF 0.001 mL/100 mL; WATER 37.307 mL/100 mL; TROLAMINE 0.11 mL/100 mL; GLYCERIN 0.3 mL/100 mL; .ALPHA.-TOCOPHEROL ACETATE 0.001 mL/100 mL

United Airlines Clean Plus Clorox

Uses:

To help decrease bacteria on skin.

Warnings:

Flammable.
Keep away from fire or flame.
For external use only.
Do not use in eyese, in case of contact, rinse eyes thoroughly with water.
Stop use and ask a doctor if skin irritation develops.

Warnings:

Keep out of reach of children.
If swallowed, get medical help or contact a Poison Control Center right away.

Directions:

Place/use enough product to cover hands, rub hands together until dry.
Supervise children in the use of the product.

Drug Facts:

Active Ingredients: Ethyl Alcohol 62% v/v

Inactive Ingredients:

Aloe Barbadensis Leaf Extract
Aqua

Carbomer
Glycerin

Propylene Glycol

Tocopheryl Acetate

Triethanolamine

Other Information:

Avoid extreme temperatures.

Purpose:

Antibacterial

PACKAGE LABEL

Does not contain bleach

DOSAGE AND ADMINISTRATION

Listed on the label: Use enough product to cover the hands